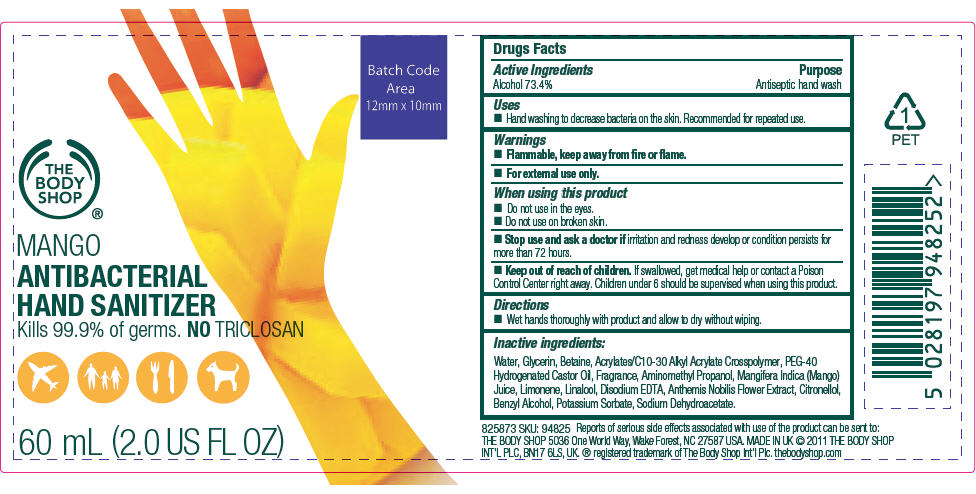 DRUG LABEL: Mango
NDC: 57691-825 | Form: GEL
Manufacturer: The Body Shop, Wake Forest
Category: otc | Type: HUMAN OTC DRUG LABEL
Date: 20111019

ACTIVE INGREDIENTS: Alcohol 0.734 g/1 mL
INACTIVE INGREDIENTS: Water; Glycerin; Betaine; Polyoxyl 40 Hydrogenated Castor Oil; Aminomethylpropanol; Mango Juice; Linalool, (+/-)-; Edetate Disodium; Chamaemelum Nobile Flower; .Beta.-Citronellol, (R)-; Benzyl Alcohol; Potassium Sorbate; Sodium Dehydroacetate; Carbomer Interpolymer Type A (55000 MPA.S); Limonene, (+/-)-

MANGO
ANTIBACTERIAL
HAND SANITIZER

Drug Facts

Active Ingredients

Alcohol 73.4%

Purpose

Antiseptic hand wash

Uses

- Hand washing to decrease bacteria on the skin. Recommended for repeated use.

Warnings

- Flammable, keep away from fire or flame.
- For external use only.

When using this product

- Do not use in the eyes.
- Do not use on broken skin.

- Stop use and ask a doctor if irritation and redness develop or condition persists for more than 72 hours.

- Keep out of reach of children. If swallowed, get medical help or contact a Poison Control Center right away. Children under 6 should be supervised when using this product.

Directions

- Wet hands thoroughly with product and allow to dry without wiping.

Inactive ingredients

Water, Glycerin, Betaine, Acrylates/C10-30 Alkyl Acrylate Crosspolymer, PEG-40 Hydrogenated Castor Oil, Fragrance, Aminomethyl Propanol, Mangifera Indica (Mango) Juice, Limonene, Linalool, Disodium EDTA, Anthemis Nobilis Flower Extract, Citronellol, Benzyl Alcohol, Potassium Sorbate, Sodium Dehydroacetate.

PRINCIPAL DISPLAY PANEL - 60 mL Bottle Label

THE
BODY
SHOP®

MANGO
ANTIBACTERIAL
HAND SANITIZER
Kills 99.9% of germs. NO TRICLOSAN

60 mL (2.0 US FL OZ)